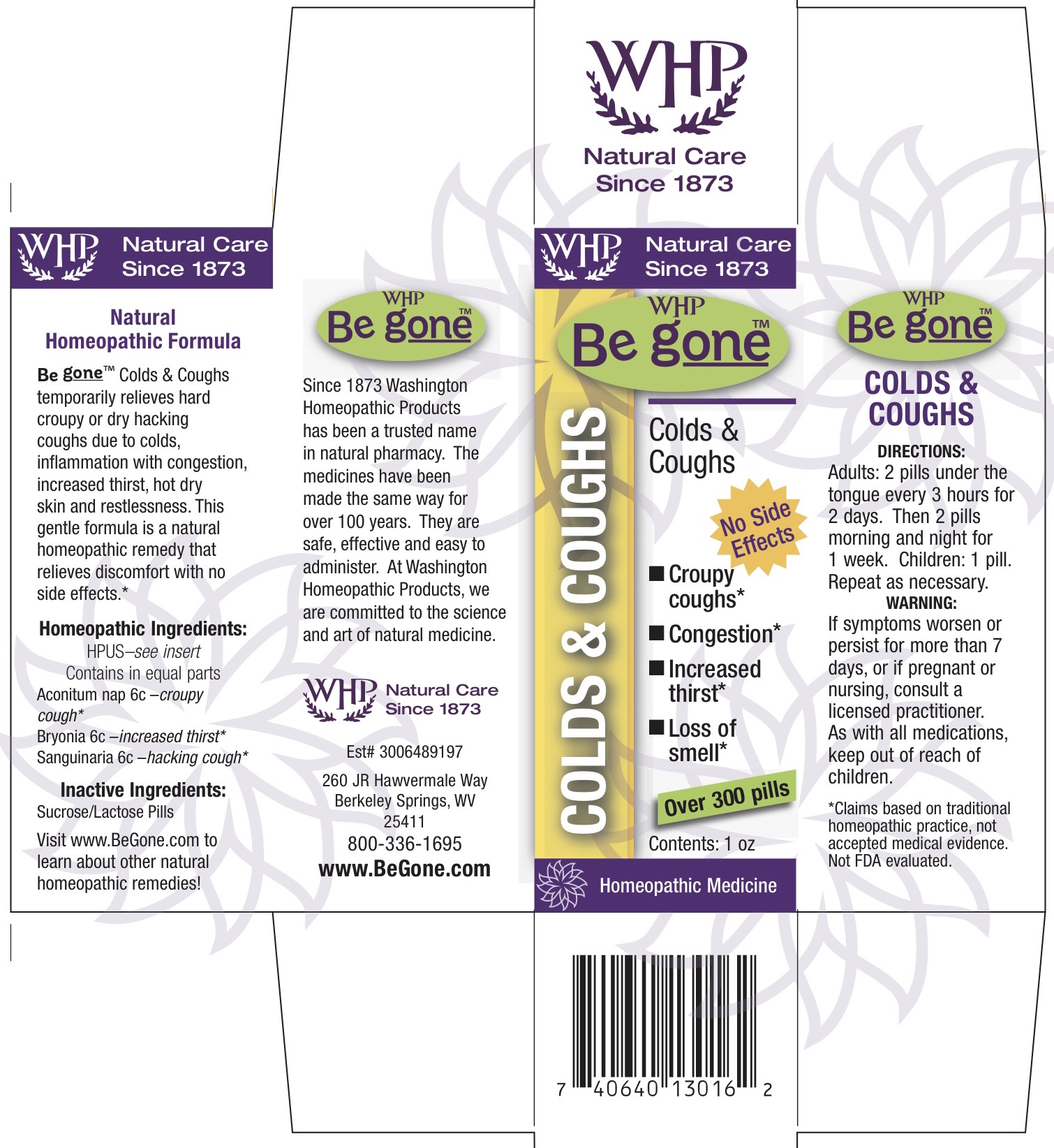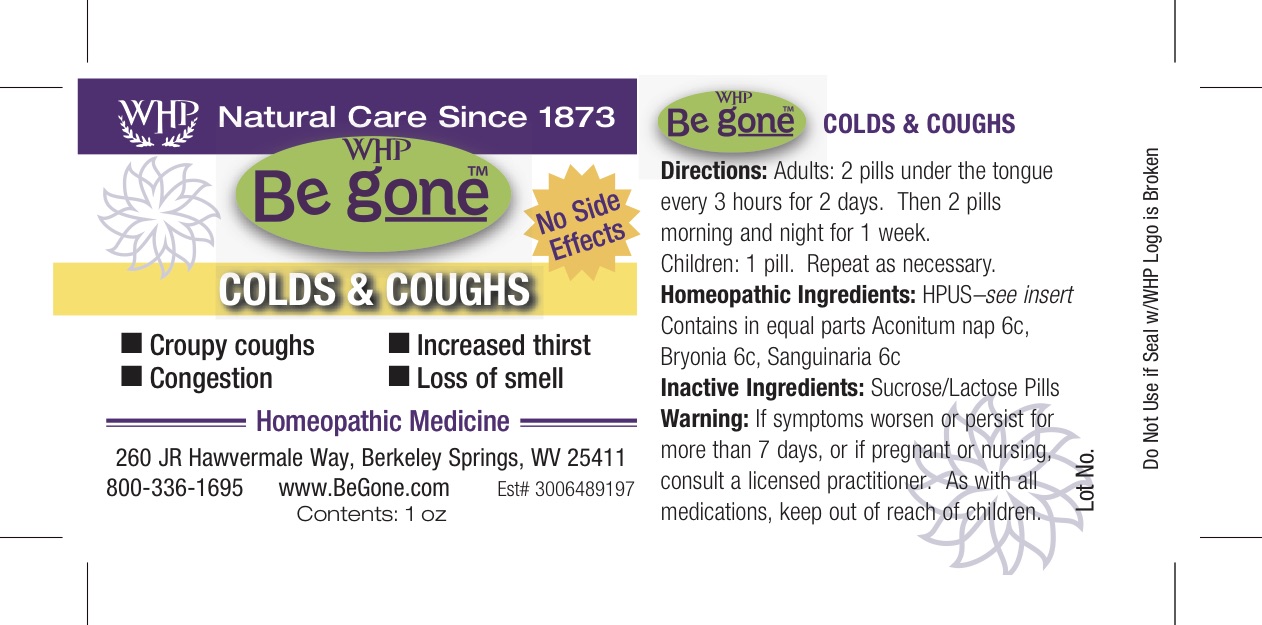 DRUG LABEL: WHP Be gone Colds and Cough
NDC: 68428-741 | Form: PELLET
Manufacturer: Washington Homeopathic Products
Category: homeopathic | Type: HUMAN OTC DRUG LABEL
Date: 20181114

ACTIVE INGREDIENTS: ACONITUM NAPELLUS 6 [hp_C]/28 g; BRYONIA ALBA ROOT 6 [hp_C]/28 g; SANGUINARIA CANADENSIS ROOT 6 [hp_C]/28 g
INACTIVE INGREDIENTS: SUCROSE; LACTOSE

DRUG FACTS

ACTIVE INGREDIENTS

ACONITUM NAP 6C

BRYONIA 6C

SANGUINARIA 6C

USES

temporarily relieves hard croupy or dry hacking coughs due to colds, inflammation with congestion, increased thirst, hot dry skin and restlessness.

KEEP OUT OF REACH OF CHILDREN

As with all medications, keep out of reach of children.

INDICATIONS

ACONITUM NAP croupy cough

BRYONIA increased thirst

SANGUINARIA hacking cough

STOP USE AND ASK DOCTOR

If symptoms persist or recur, discontinue use. If pregnant or nursing a baby, consult a licensed practitioner before using this product.

DIRECTIONS

Adults 2 pills every 3 hours for 2 days. Then 2 pills morning and night for 2 weeks.

Children: 1 pills. Repeat as necessary.

INACTIVE INGREDIENTS

Sucrose/Lactose

PRINCIPAL DISPLAY PANEL

WHP Be g oneTM Colds and Cough label

WHP Be g oneTM Colds and Cough box